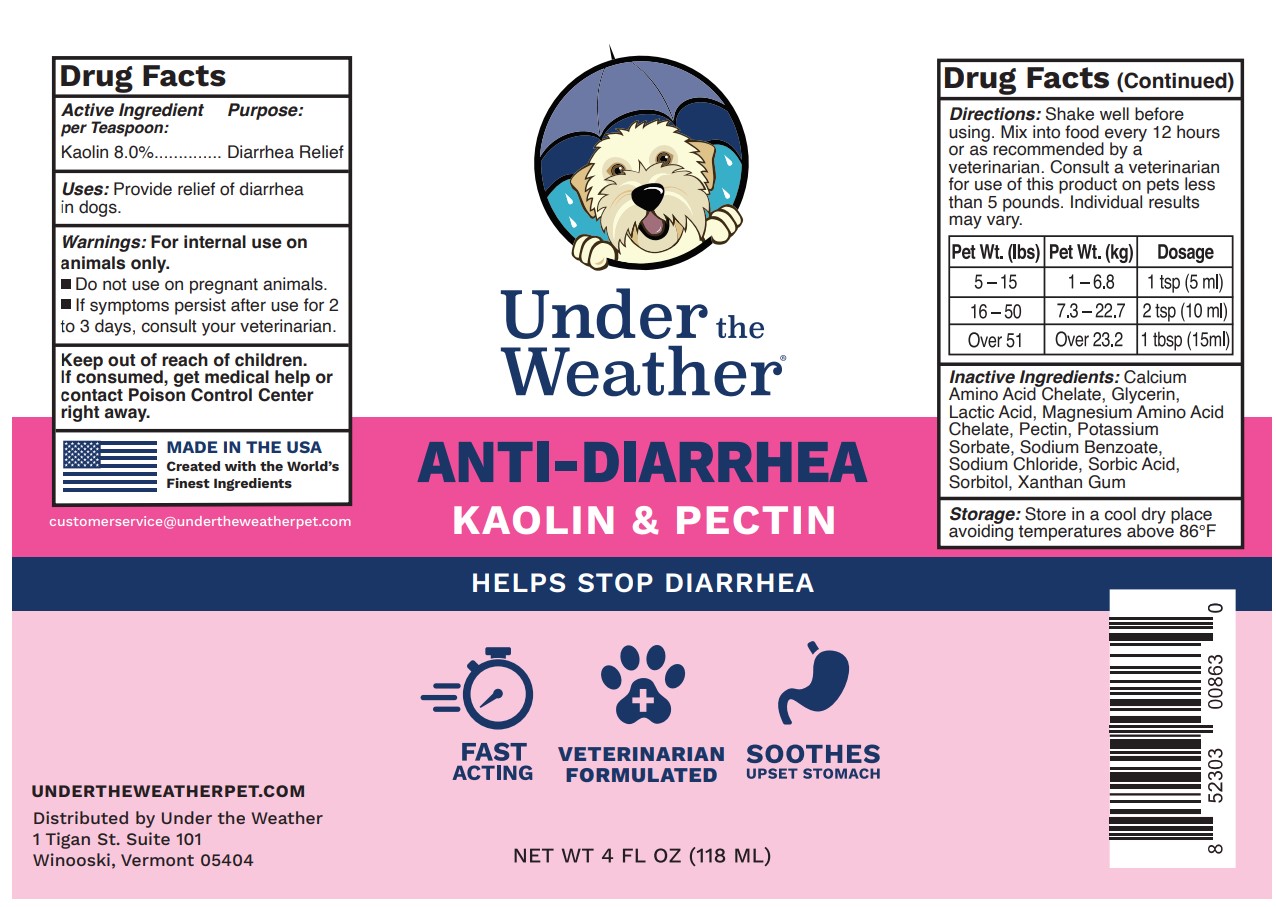 DRUG LABEL: UNDER THE WEATHER ANTI DIARRHEA
NDC: 86192-863 | Form: SOLUTION
Manufacturer: UNDER THE WEATHER
Category: animal | Type: OTC ANIMAL DRUG LABEL
Date: 20231121

ACTIVE INGREDIENTS: KAOLIN 8 g/100 mL
INACTIVE INGREDIENTS: Pectin; WATER; GLYCERIN; SORBIC ACID; XANTHAN GUM; SORBITOL; SODIUM BENZOATE; POTASSIUM SORBATE; CALCIUM; MAGNESIUM; SODIUM CHLORIDE; LACTIC ACID

UNDER THE WEATHER ANTI DIARRHEA 4OZ

ACTIVE INGREDIENTS PER TEASPOON

KAOLIN 8.0%

PURPOSE

DIARRHEA RELIEF

WARNINGS

FOR INTERNAL USE IN ANIMALS. DO NOT USE ON PREGNANT ANIMALS. IF SYMPTOMS PERSIST AFTER USE FOR 2 TO 3 DAYS, CONSULT YOUR VETERINARIAN.